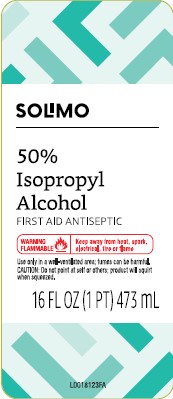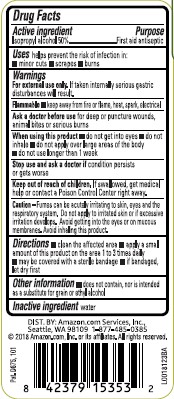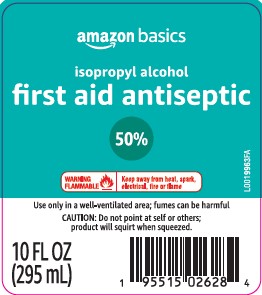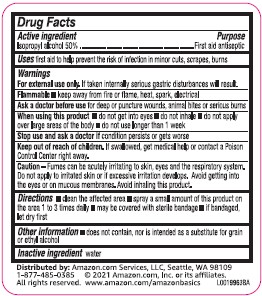 DRUG LABEL: 50% Isopropyl Alcohol
NDC: 72288-864 | Form: SOLUTION
Manufacturer: Amazon.Com Services LLC
Category: otc | Type: HUMAN OTC DRUG LABEL
Date: 20251113

ACTIVE INGREDIENTS: ISOPROPYL ALCOHOL 500 mg/1 mL
INACTIVE INGREDIENTS: WATER

Basics_Solimo_864.003/864AA-AC
50% Isopropyl Alcohol

Active ingredient

Isopropyl alcohol 50%

Purpose

First Aid Antiseptic

Uses

first aid to help prevent the risk of infection in minor cuts, scrapes, burns

Warnings

For external use only. If taken internally serioun gastric disturbances will result.

Flammable, keep away from fire or flame, heat, spark, electrical.

Ask a doctor before use if you have

deep or pucture wounds, animal bites or serious burns

When using this product

- do not get into eyes
- do not inhale
- do not apply over large areas of the body
- do not use longer than 1 week

Stop use and ask a doctor if

condition persists or gets worse

Keep out of reach of children.

If swallowed, get medical help or contact a Poison Control Center right away.

Caution

Fumes can be acutely irritating to skin, eyes and the respiratory system. Do not apply to irritated skin or if excessive irritatation develops. Avoid getting into the eyes or on mucous membranes. Avoid inhaling this product.

Directions

- clean the affected area
- spray a small amount of the product on the affected area 1 to 3 times a day
- may be covered with a sterile bandage
- if bandaged, let dry first

Other information

- does not contain, nor is intended as a substitute for grain or ethyl alcohol

Inactive ingredient

water

ADVERSE REACTION

DISTRIBUTED BY: Amazon.com, Services, LLC, Seattle, WA 98109

1-877-485-0385 ©2021 Amazon.com, Inc. or its affiliates.

All rights reserved. www.amazon.com/amazonbasics

Principal display panel

SOLIMO

50% Isopropyl Alcohol

First Aid Antiseptic

WARNING FLAMMABLE - Keep away from heat, spark, electrical, fire or flame

Use ony in a well-ventilated area. Fumes can be harmful

CAUTION: Do not point at self or others; product will squirt when squeezed.

discard sealed & empty before recycling. Plastic bottle. how2recycle.info

16 FL OZ (1 PT) 473 mL

Principal display panel

amazon basics

isopropyl alcohol

first aid antiseptic

50%

WARNING FLAMMABLE - Keep away from heat, spark, electrical, fire or flame

Use only in a well-ventilated area; fumes can be harmful

CAUTION: Do not point at self or others; product will squirt when squeezed

10 FL OZ (295 mL)